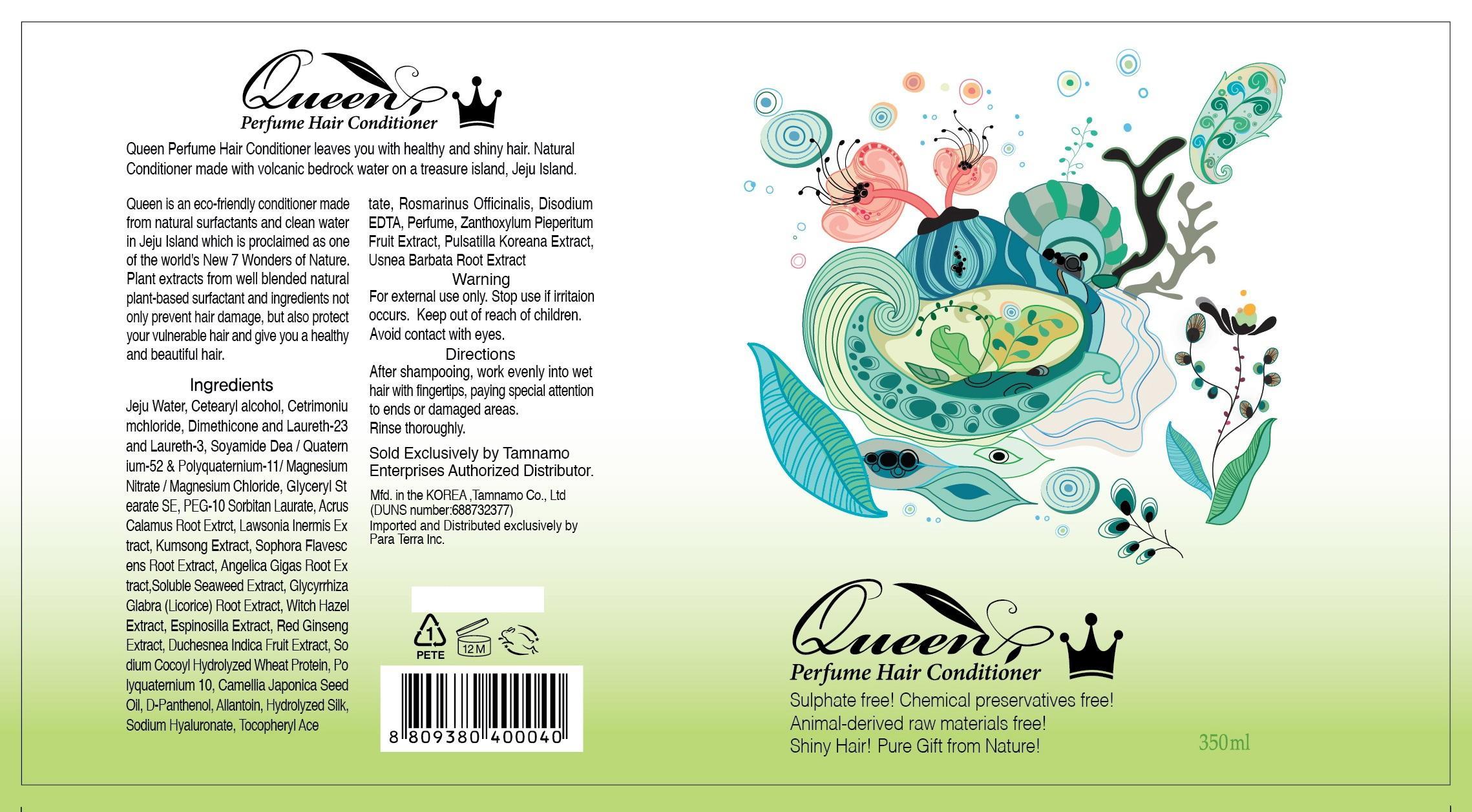 DRUG LABEL: Queen Perfume Hair Conditioner
NDC: 60344-6001 | Form: LIQUID
Manufacturer: Tamnamo Co., Ltd
Category: otc | Type: HUMAN OTC DRUG LABEL
Date: 20140130

ACTIVE INGREDIENTS: ALLANTOIN 0.02 mg/1 mL
INACTIVE INGREDIENTS: CETOSTEARYL ALCOHOL; GLYCERYL MONOSTEARATE; SOPHORA FLAVESCENS ROOT; ANGELICA GIGAS ROOT; GLYCYRRHIZA GLABRA; HYALURONATE SODIUM

Drug Facts

ACTIVE INGREDIENT

allantoin

INACTIVE INGREDIENT

Jeju Water, Cetearyl alcohol, Cetrimoniumchloride, Dimethicone and Laureth-23 and Laureth-3, SOYAMIDE DEA QUATERNIUM-52 POLYQUATERNIUM-11 MAGNESIUM NITRATE MAGNESIUM CHLORIDE, Glyceryl Stearate SE, PEG-10 Sorbitan Laurate , Acrus Calamus Root Extrct, Lawsonia Inermis Extract, Kumsong Extract, Sophora Flavescens Root Extract, Angelica Gigas Root Extract, Soluble Seaweed Extract, Glycyrrhiza Glabra (Licorice)Root Extract, Witch Hazel Extract, Espinosilla Extract, Red Ginseng Extract, Duchesnea Indica Fruit Extract, Sodium Cocoyl Hydrolyzed Wheat Protein, Polyquaternium 10, Camellia Japonica Seed Oil, D-Panthenol, Allantoin, Hydrolyzed Silk, Sodium Hyaluronate, Tocopheryl Acetate, Rosmarinus Officinalis, Disodium EDTA, Perfume, Zanthoxylum Pieperitum Fruit Extract, Pulsatilla Koreana Extract, Usnea Barbata Root Extract

PURPOSE

supplying moisture and nutrient to scalp and hair

keep out of reach of the children

INDICATIONS AND USAGE

after shampooing, work evenly into wet hair with fingertips, paying special attention to ends or damaged areas
rinse thoroughly

stop use if irritation occurs
avoid contact with eyes

DOSAGE AND ADMINISTRATION

for external use only